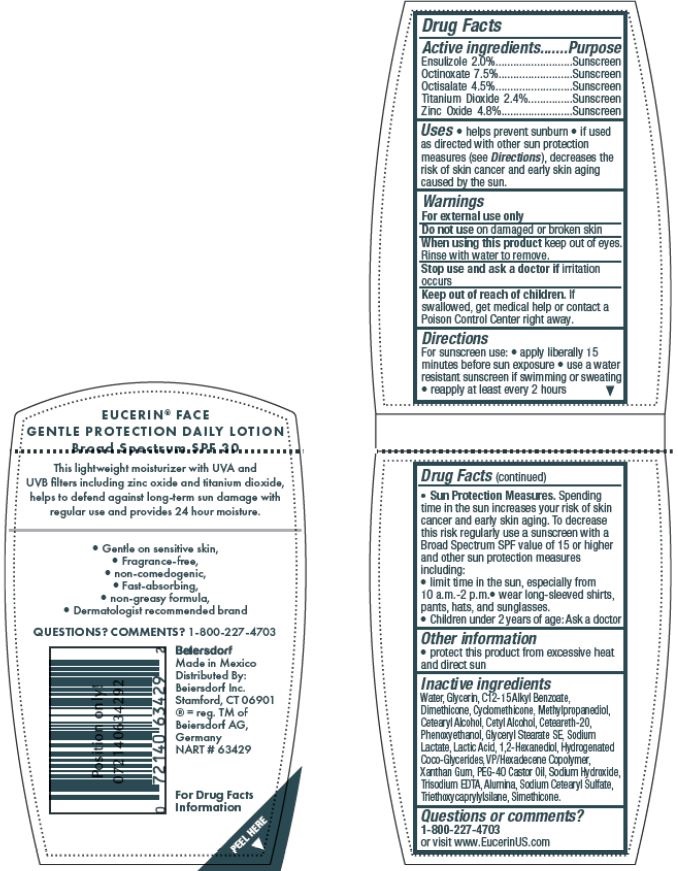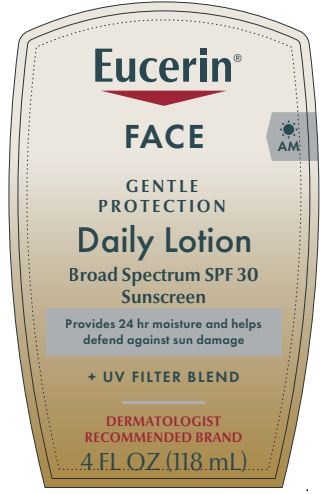 DRUG LABEL: Eucerin Daily Protection Face
NDC: 10356-323 | Form: LOTION
Manufacturer: Beiersdorf Inc
Category: otc | Type: HUMAN OTC DRUG LABEL
Date: 20251216

ACTIVE INGREDIENTS: ENSULIZOLE 2 g/100 mL; OCTINOXATE 7.5 g/100 mL; OCTISALATE 4.5 g/100 mL; TITANIUM DIOXIDE 2.4 g/100 mL; ZINC OXIDE 4.8 g/100 mL
INACTIVE INGREDIENTS: WATER; GLYCERIN; ALKYL (C12-15) BENZOATE; DIMETHICONE; CYCLOMETHICONE; CETYL ALCOHOL; CETOSTEARYL ALCOHOL; POLYOXYL 20 CETOSTEARYL ETHER; GLYCERYL MONOSTEARATE; SODIUM LACTATE; LACTIC ACID; COCO-GLYCERIDES; POLYOXYL 40 CASTOR OIL; SODIUM CETOSTEARYL SULFATE; XANTHAN GUM; EDETATE TRISODIUM; SODIUM HYDROXIDE; ALUMINUM OXIDE; PHENOXYETHANOL; METHYLPROPANEDIOL; 1,2-HEXANEDIOL; VINYLPYRROLIDONE/HEXADECENE COPOLYMER; TRIMETHOXYCAPRYLYLSILANE

Eucerin Daily Protection Face

Active ingredients
Ensulizole 2%
Octinoxate 7.5%
Octisalate 4.5%
Titanium Dioxide 2.4%
Zinc Oxide 4.8%

Purpose
Sunscreens

Uses
• helps prevent sunburn • if used as directed with other sun protection
measures (see Directions), decreases the risk of skin cancer and early skin aging
caused by the sun.

Warnings
For external use only

Do not use on damaged or broken skin

When using this product keep out of eyes.
Rinse with water to remove

Stop use and ask a doctor if irritation occurs

Keep out of reach of children. If swallowed,
get medical help or contact a Poison Control
Center right away.

Directions
For sunscreen use: • apply liberally 15
minutes before sun exposure • use a water
resistant sunscreen if swimming or sweating
• reapply at least every 2 hours
• Sun Protection Measures. Spending time in
the sun increases your risk of skin cancer and
early skin aging. To decrease this risk regularly
use a sunscreen with a Broad Spectrum SPF
value of 15 or higher and other sun protection
measures including:
• limit time in the sun, especially from
10 a.m.-2 p.m.• wear long-sleeved shirts,
pants, hats, and sunglasses.
• Children under 6 months of age: Ask a doctor

Inactive Ingredients

Water, Glycerin, C12-15 Alkyl Benzoate,

Dimethicone, Cyclomethicone, Methylpropanediol,

Cetearyl Alcohol, Cetyl Alcohol, Ceteareth-20,

Phenoxyethanol, Glyceryl Stearate SE, Sodium

Lactate, Lactic Acid, 1,2-Hexanediol,

Hydrogenated Coco-Glycerides,

VP/Hexadecene Copolymer, Xanthan Gum,

PEG-40 Castor Oil, Sodium Hydroxide,

Trisodium EDTA, Alumina, Sodium Cetearyl

Sulfate, Triethoxycaprylylsilane, Simethicone

Questions or comments

1-800-227-4703

PACKAGE LABEL

Eucerin

Face

Gentle Protection Daily Lotion
Broad Spectrum SPF 30 Sunscreen

Provides 24 hour Moisture and helps

defend against sun damage

UV filter Blend

Dermatologist Recommended Brand